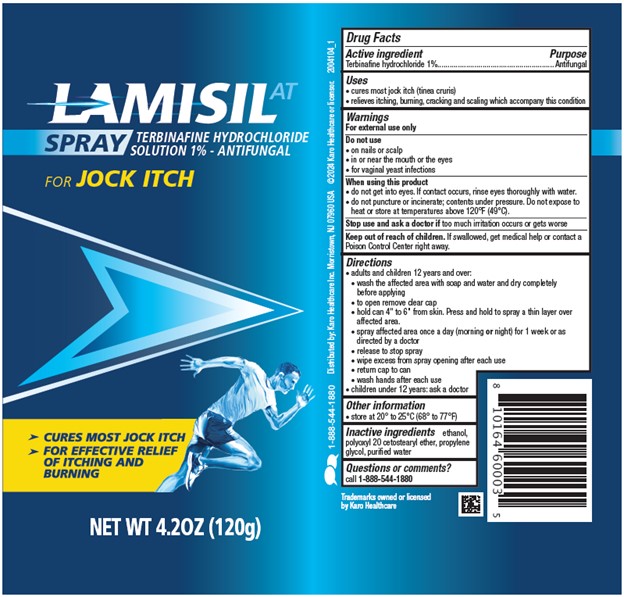 DRUG LABEL: Lamisil AT
NDC: 84485-3606 | Form: SPRAY
Manufacturer: Karo Healthcare Inc.
Category: otc | Type: HUMAN OTC DRUG LABEL
Date: 20251212

ACTIVE INGREDIENTS: TERBINAFINE HYDROCHLORIDE 1 g/100 g
INACTIVE INGREDIENTS: WATER; ALCOHOL; PROPYLENE GLYCOL; POLYOXYL 20 CETOSTEARYL ETHER

Lamisil AT (Terbinafine Hydrochloride) Spray 1% 120 g

Active Ingredient

Terbinafine hydrochloride 1%

Purpose

Antifungal

Uses

- cures most jock itch (tinea cruris)
- relieves itching, burning, cracking and scaling which accompany this condition

Warnings

For external use only

Do not use

- on nails or scalp
- in or near the mouth or eyes
- for vaginal yeast infections

When using this product

- do not get into eyes. If eye contact occurs, rinse thoroughly with water.
- do not puncture or incinerate; contents under pressure. Do not expose to heat or store at temperatures above 120°F (49°C).

Stop use and ask a doctor if too much irritation occurs or gets worse

Keep out of reach of children. If swallowed, get medical help or contact a Poison Control Center right away.

Directions

- adults and children 12 years and over:
  - wash the affected area with soap and water and dry completely before applying
  - to open remove clear cap
  - hold can 4" to 6" from skin. Press and hold to spray a thin layer over affected area.
  - Spray affected area once a day (morning or night) for 1 week or as directed by a doctor
  - release to stop spray
  - wipe excess from spray opening after each use
  - return cap to can
  - wash hands after each use
- children under 12 years: ask a doctor

Other Information

- store at 20° to 25°C (68° to 77°F)

Inactive Ingredients

ethanol, polyoxyl 20 cetostearyl ether, propylene glycol, purified water

Questions or comments?

call 1-888-544-1880

PACKAGE LABEL.PRINCIPAL DISPLAY

LAMISILAT
SPRAY
TERBINAFINE HYDROCHLORIDE
SOLUTION 1% - ANTIFUNGAL
FOR JOCK ITCH
►CURES MOST JOCK ITCH

►FOR EFFECTIVE RELIEF OF ITCHING AND BURNING

NET WT 4.20Z (120g)
1-888-544-1880

Distributed By:
Karo Healthcare Inc.
Morristown, NJ 07960 USA

Trademarks owned or licensed
by Karo Healthcare

©2024 Karo Healthcare or licensor
2004104_1